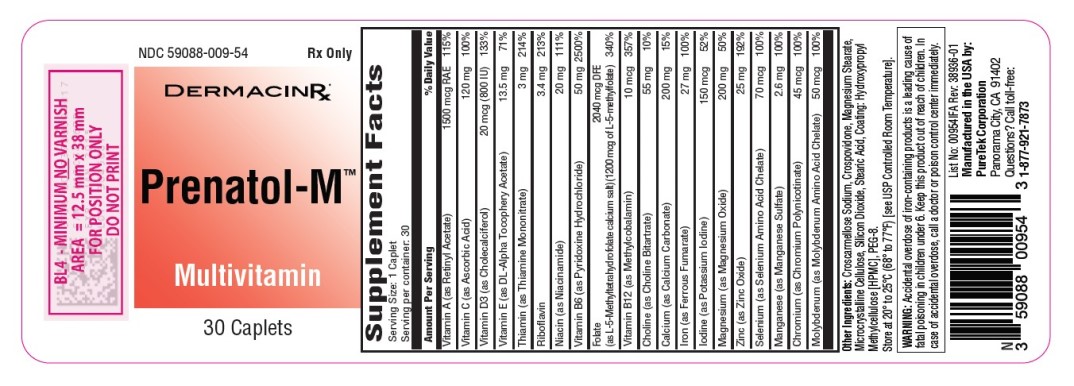 DRUG LABEL: Prenatol-M
NDC: 59088-009 | Form: TABLET
Manufacturer: PureTek Corporation
Category: prescription | Type: HUMAN PRESCRIPTION DRUG LABEL
Date: 20240506

ACTIVE INGREDIENTS: CHOLECALCIFEROL 20 ug/1 1; FERROUS FUMARATE 27 mg/1 1; MOLYBDENUM 50 ug/1 1; ASCORBIC ACID 120 mg/1 1; ZINC OXIDE 25 mg/1 1; CHOLINE BITARTRATE 55 mg/1 1; RIBOFLAVIN 3.4 mg/1 1; MAGNESIUM OXIDE 200 mg/1 1; .ALPHA.-TOCOPHEROL ACETATE, DL- 13.5 mg/1 1; VITAMIN A ACETATE 1500 ug/1 1; SELENIUM 70 ug/1 1; NIACINAMIDE 20 mg/1 1; PYRIDOXINE HYDROCHLORIDE 50 mg/1 1; CALCIUM CARBONATE 200 mg/1 1; CHROMIUM NICOTINATE 45 ug/1 1; MANGANESE SULFATE 2.6 mg/1 1; POTASSIUM IODIDE 150 ug/1 1; METHYLCOBALAMIN 10 ug/1 1; LEVOMEFOLATE CALCIUM 2040 ug/1 1; THIAMINE MONONITRATE 3 mg/1 1
INACTIVE INGREDIENTS: STEARIC ACID; HYPROMELLOSES; MICROCRYSTALLINE CELLULOSE; MAGNESIUM STEARATE; CROSPOVIDONE; CROSCARMELLOSE SODIUM; SILICON DIOXIDE; POLYETHYLENE GLYCOL 400

Prenatol-M

DESCRIPTION:

Each caplet contains:
Vitamin A (as Retinyl Acetate) ………………....… 1500 mcg RAE
Vitamin C (as Ascorbic Acid) ………………….………… 120 mg
Vitamin D3 (as Cholecalciferol).……………....... 20 mcg (800 IU)
Vitamin E (as Dl-Alpha Tocopheryl Acetate) ….......….…. 13.5 mg
Thiamin (as Thiamine Mononitrate) …………...…………… 3 mg
Riboflavin ……………………….…………………….…. 3.4 mg
Niacin (as Niacinamide) ………………..……………….… 20 mg
Vitamin B6 (as Pyridoxine Hydrochloride) …....…………... 50 mg
Folate (as L-5-Methyltetrahydrofolate calcium salt) ….... 2040 mcg DFE
(1200 mcg as L-5-Methylfolate)
Vitamin B12 (as Methylcobalamin) ……….……………... 10 mcg
Choline (as Choline Bitartrate) …….……………………… 55 mg
Calcium (as Calcium Carbonate) ……...…………………. 200 mg
Iron (as Ferrous Fumarate) ………..……………………… 27 mg
Iodine (as Potassium Iodine) …...……………………….150 mcg
Magnesium (as Magnesium Oxide) …...………………… 200 mg
Zinc (as Zinc Oxide) ………………...…………………….. 25 mg
Selenium (as Selenium Amino Acid Chelate) ……………. 70 mcg
Manganese (as Manganese Sulfate) ……………………… 2.6 mg
Chromium (as Chromium Polynicotinate) ……………….. 45 mcg
Molybdenum (as Molybdenum Amino Acid Chelate)…...… 50 mcg

Other Ingredients:

Croscarmellose Sodium, Crospovidone, Magnesium Stearate, Microcrystalline Cellulose, Silicon Dioxide, Stearic Acid, Coating: Hydroxypropyl Methylcellulose [HPMC], PEG-8.

Indications and Usage: Prenatol-M™ is indicated to provide vitamins and minerals to women throughout pregnancy and during the postnatal period for both lactating and non-lactating mothers, and throughout the childbearing years.

Prenatol-M™ may be beneficial in improving the nutritional status of women prior to conception.

Contraindications:

This product is contraindicated in patients with known hypersensitivity to any of its ingredients; also, all iron compounds are contraindicated in patients with hemosiderosis, hemochromatosis, or hemolytic anemias. Pernicious anemia is a contraindication, as folate may obscure its signs and symptoms.

Warnings:

Accidental overdose of iron-containing products is a leading cause of fatal poisoning in children under 6. In case of accidental overdose, call a doctor or poison control center immediately. Administration of folate alone is improper therapy for pernicious anemia and other megaloblastic anemias in which vitamin B12 is deficient.

Precautions:

Folate in doses above 0.1 mg daily may obscure pernicious anemia, in that hematologic remission can occur while neurological manifestations remain progressive. There is a potential danger in administering folate to patients with undiagnosed anemia since folic acid may obscure the diagnosis of pernicious anemia by alleviating the hematologic manifestations of the disease while allowing the neurologic complications to progress. This may result in severe nervous system damage before the correct diagnosis is made. Adequate doses of vitamin B12 may prevent, halt, or improve the neurologic changes caused by pernicious anemia. The patient’s medical conditions and consumption of other drugs, herbs, and/or supplements should be considered.

For use on the order of a licensed healthcare practitioner. Call your doctor about side effects. To report side effects, call PureTek
Corporation at 1-877-921-7873 or FDA at 1-800-FDA-1088 or www.fda.gov/medwatch.

Drug Interactions:

Prenatol-M™ is not recommended for and should not be given to patients receiving levodopa because the action of levodopa is antagonized by pyridoxine. There is a possibility of increased bleeding due to pyridoxine interaction with anticoagulants (e.g., Aspirin, Heparin, or Clopidogrel).

Adverse Reactions:

Folate: Allergic sensitizations have been reported following both oral and parenteral administration of folate.

Ferrous Fumarate: Gastrointestinal disturbances (anorexia, nausea, diarrhea, constipation) occur occasionally but are usually mild and may subside with continuation of therapy. Although the absorption of iron is best when taken between meals, giving Prenatol-M™ after meals may control occasional gastrointestinal disturbances. Prenatol-M™ is best absorbed when taken at bedtime.

Adverse reactions have been reported with specific vitamins and minerals but generally at levels substantially higher than those contained herein. However, allergic, and idiosyncratic reactions are possible at lower levels. Iron, even at the usual recommended levels, has been associated with gastrointestinal intolerance in some patients.

Overdose:

Iron: signs and symptoms: Iron is toxic. Acute overdosage of iron may cause nausea and vomiting and, in severe cases, cardiovascular collapse and death. Other symptoms include pallor and cyanosis,melena, shock, drowsiness and coma. The estimated overdose of orally ingested iron is 300 mg/kg body weight. When overdoses are ingested by children, severe reactions, including fatalities, have resulted. Prenatol-M™ should be stored beyond the reach of children to prevent against accidental iron poisoning. Keep this and all other drugs out of the reach of children.

Treatment:

For specific therapy, exchange transfusion and chelating agents should be used. For general management, gastric lavage with sodium bicarbonate solution or milk. Administer intravenous fluids and electrolytes and use oxygen.

Dosage and Administration:

Prenatol-M™ caplet daily, between meals or as directed by a licensed healthcare practitioner. Do not administer to children under
the age of 12.

How Supplied:

Prenatol-M™ are beige speckled, oblong, coated caplets, supplied in a bottle containing 30 caplets (NDC 59088-009-54). Dispense in a tight, light-resistant container as defined in the USP/NF with a child resistant closure.

Storage

Do not use if bottle seal is broken.
KEEP THIS AND ALL MEDICATIONS OUT OF THE REACH OF CHILDREN.
Store at 20° to 25°C (68° to 77°F) [see USP Controlled Room Temperature].

Prenatol-M™

Manufactured in the USA by:

PureTek Corporation
Panorama City, CA 91402
For questions or information
call toll-free: 877-921-7873